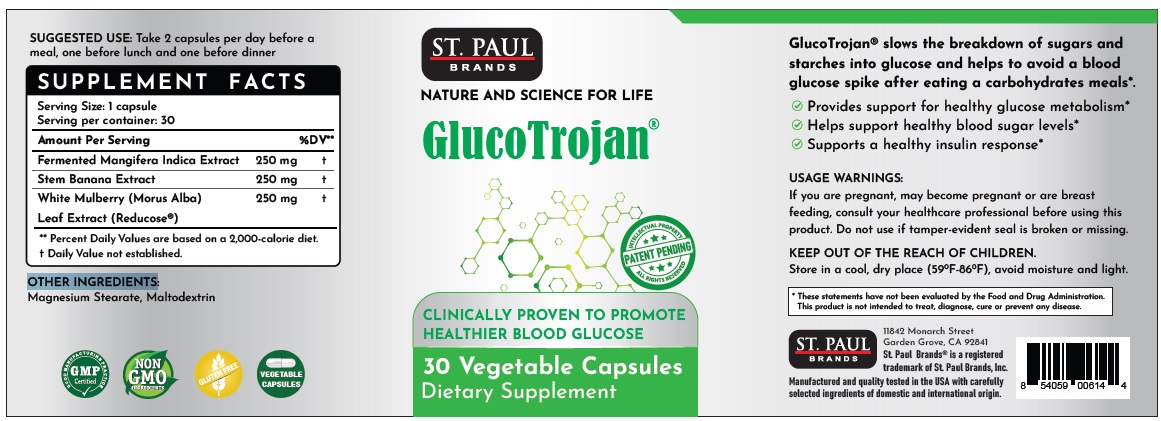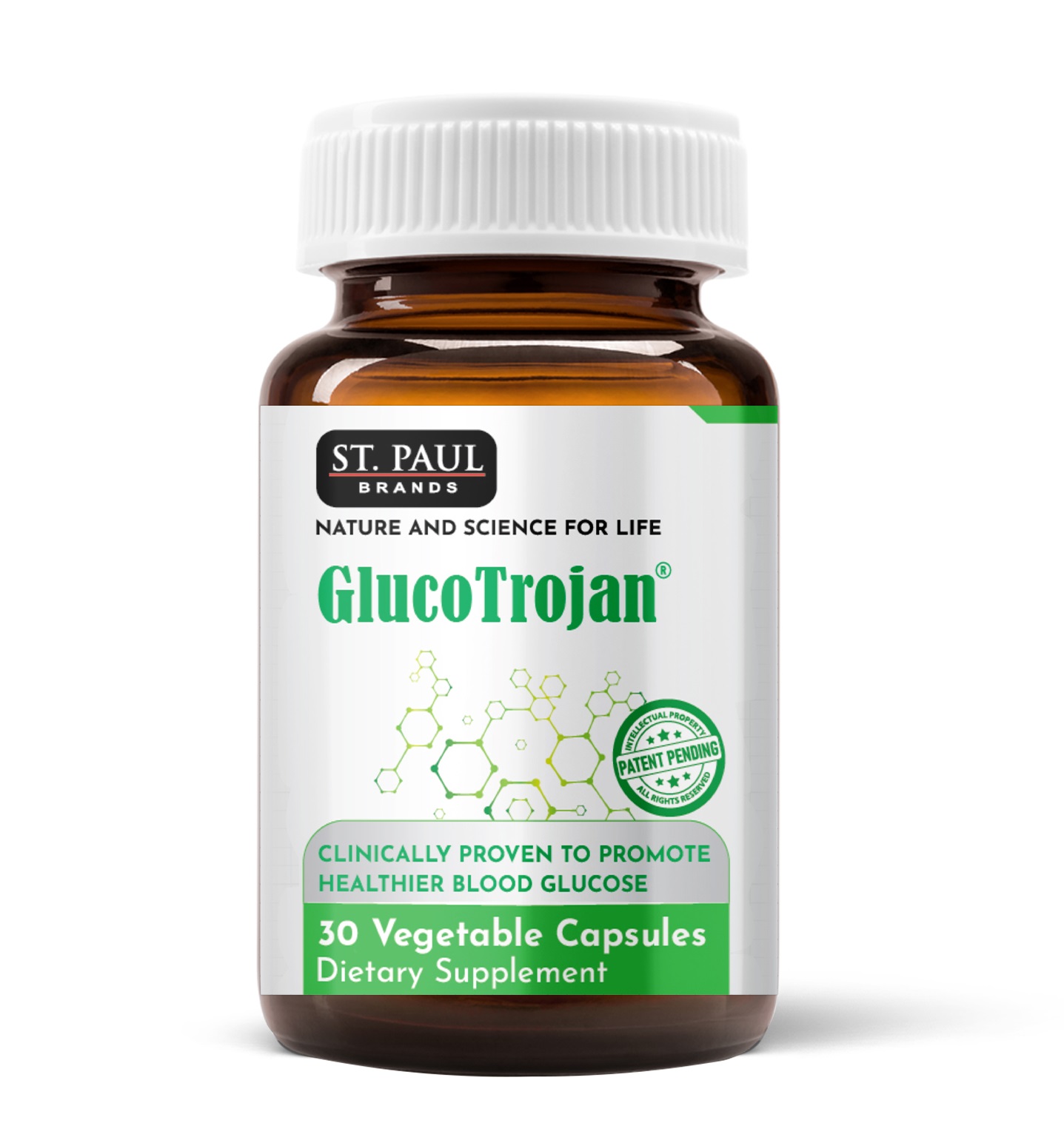 DRUG LABEL: St. Paul Brands GlucoTrojan
NDC: 13411-860 | Form: CAPSULE
Manufacturer: Advanced Pharmaceutical Services, Inc. Dba Affordable Quality Pharmaceuticals
Category: otc | Type: HUMAN OTC DRUG LABEL
Date: 20250331

ACTIVE INGREDIENTS: MANGIFERA INDICA LEAF 250 mg/1 1; BANANA 250 mg/1 1; MORUS ALBA LEAF 250 mg/1 1
INACTIVE INGREDIENTS: MALTODEXTRIN; MAGNESIUM STEARATE

Identity

Dietary supplement

Warnings

If you are pregnant, may become pregnant or are breast feeding, consult your healthcare professional before using this product. Do not use if tamper-evident seal is broken or missing.

Direction

Take 2 capsules per day before a meal, one before lunch and one before dinner.

Safe handling warning

Store in a cool, dry place (59oF-86oF), avoid moisture and light.

HEALTH CLAIM

GLUCOTROJAN
Clinically Proven to Promote Healthier Blood Glucose

GlucoTrojan® slows the breakdown of sugars and starches into glucose and helps to avoid a blood glucose spike after eating a carbohydrates meal.*

- Provides support for healthy glucose metabolism*
- Helps support healthy blood sugar levels*
- Supports a healthy insulin response*

* These statements have not been evaluated by the Food & Drug Administration. This product is not intended to diagnose, treat, cure, or prevent any disease.

Other Ingredients

Magnesium Stearate, Maltodextrin